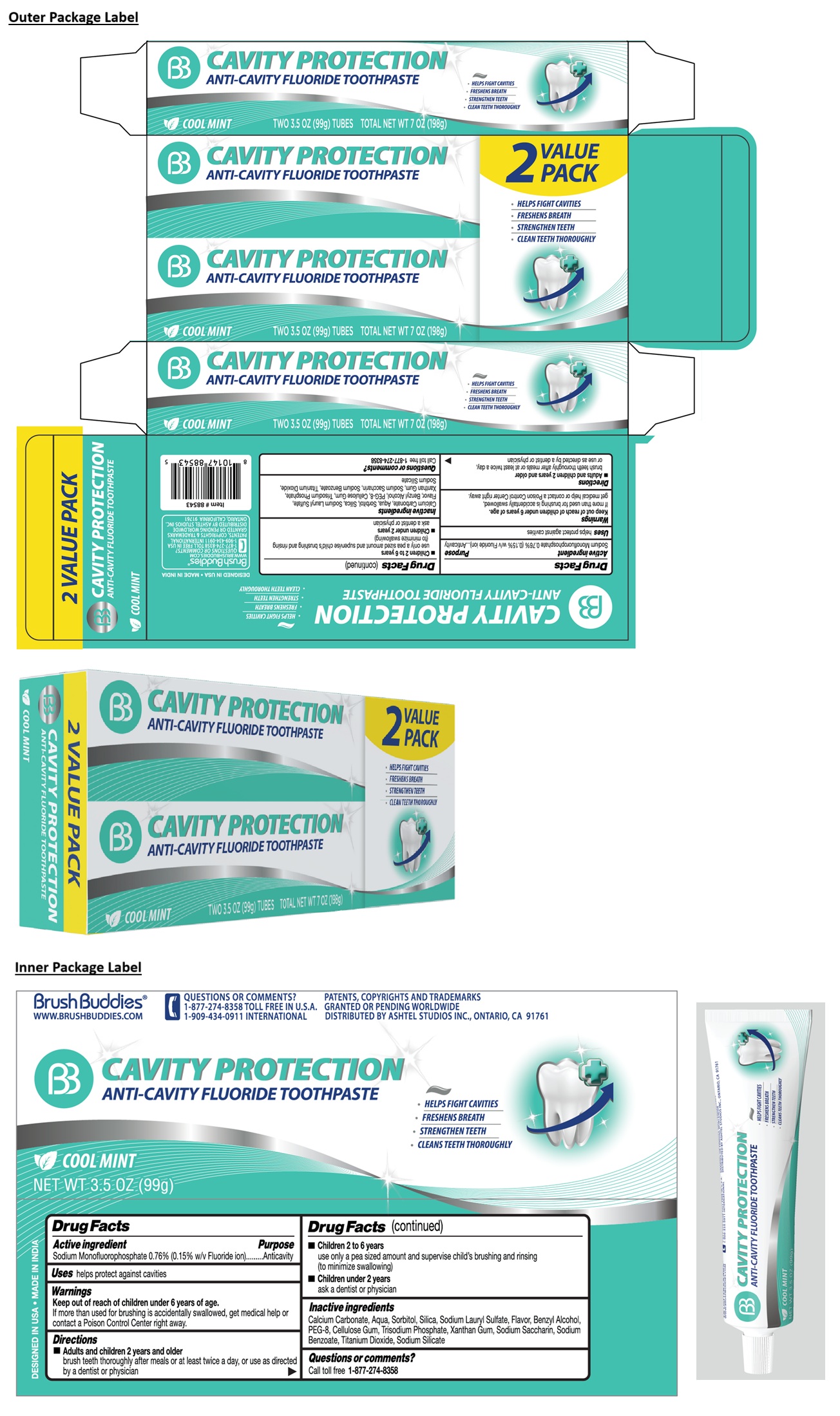 DRUG LABEL: Brush Buddies 2 VALUE PACK CAVITY PROTECTION ANTI-CAVITY FLUORIDE
NDC: 70108-185 | Form: PASTE, DENTIFRICE
Manufacturer: Ashtel Studios, Inc.
Category: otc | Type: HUMAN OTC DRUG LABEL
Date: 20250813

ACTIVE INGREDIENTS: SODIUM MONOFLUOROPHOSPHATE 0.15 g/100 g
INACTIVE INGREDIENTS: CALCIUM CARBONATE; WATER; SORBITOL; SILICON DIOXIDE; SODIUM LAURYL SULFATE; BENZYL ALCOHOL; POLYETHYLENE GLYCOL 400; CARBOXYMETHYLCELLULOSE SODIUM, UNSPECIFIED; SODIUM PHOSPHATE, TRIBASIC, ANHYDROUS; XANTHAN GUM; SACCHARIN SODIUM; SODIUM BENZOATE; TITANIUM DIOXIDE; SODIUM SILICATE

Brush Buddies® 2 VALUE PACK CAVITY PROTECTION ANTI-CAVITY FLUORIDE TOOTHPASTE

Active ingredient

Sodium Monofluorophosphate 0.76% (0.15% w/v Fluoride ion)

Purpose

Anticavity

Uses

helps protect against cavities

Warnings

Keep out of reach of children under 6 years of age.
If more than used for brushing is accidentally swallowed, get medical help or contact a Poison Control Center right away.

Directions

• Adults and children 2 years and older
brush teeth thoroughly after meals or at least twice a day, or use as directed by a dentist or physician

• Children 2 to 6 years
use only a pea sized amount and supervise child's brushing and rinsing (to minimize swallowing)

• Children under 2 years
ask a dentist or physician

Inactive ingredients

Calcium Carbonate, Aqua, Sorbitol, Silica, Sodium Lauryl Sulfate, Flavor, Benzyl Alcohol, PEG-8, Cellulose Gum, Trisodium Phosphate, Xanthan Gum, Sodium Saccharin, Sodium Benzoate, Titanium Dioxide, Sodium Silicate

Questions or comments?

Call toll free 1-877-274-8358

• HELPS FIGHT CAVITIES

• FRESHENS BREATH

• STRENGTHEN TEETH

• CLEANS TEETH THOROUGHLY

DESIGNED IN USA • MADE IN INDIA

WWW.BRUSHBUDDIES.COM

1-909-434-0911 INTERNATIONAL

PATENTS, COPYRIGHTS & TRADEMARKS GRANTED OR PENDING WORLDWIDE

DISTRIBUTED BY ASHTEL STUDIOS INC.
ONTARIO, CALIFORNIA 91761